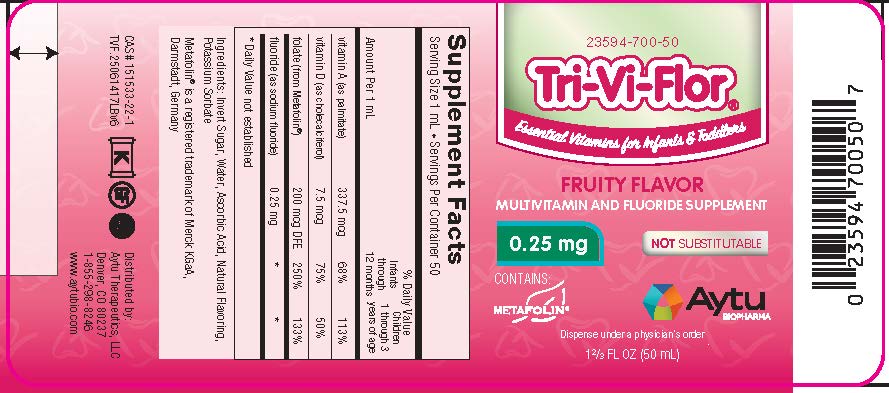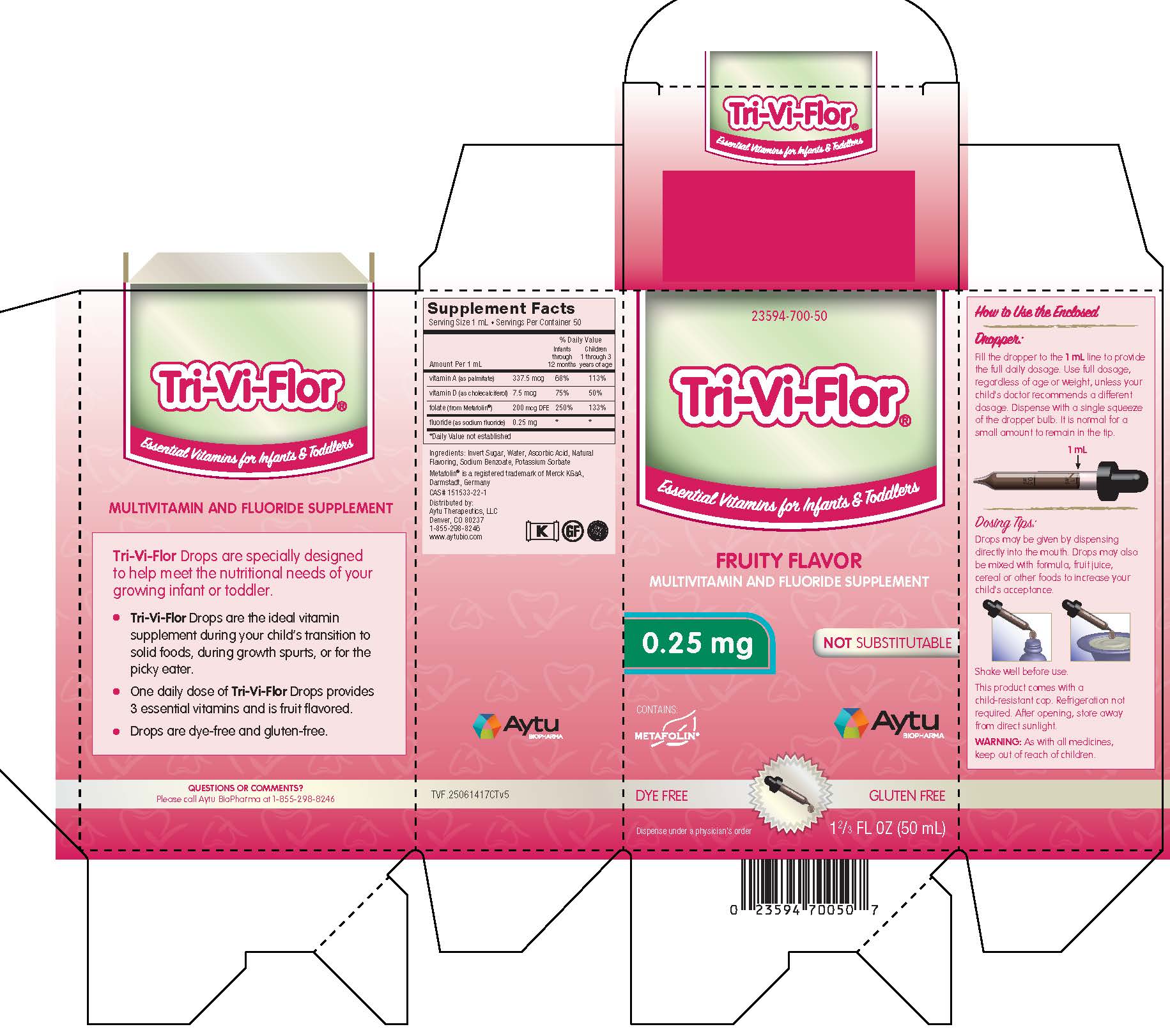 DRUG LABEL: Tri-Vi-Flor
NDC: 23594-700 | Form: SUSPENSION/ DROPS
Manufacturer: Aytu Therapeutics LLC
Category: other | Type: DIETARY SUPPLEMENT
Date: 20230929

ACTIVE INGREDIENTS: VITAMIN A PALMITATE 337.5 ug/1 mL; CHOLECALCIFEROL 7.5 ug/1 mL; LEVOMEFOLATE CALCIUM 200 ug/1 mL; SODIUM FLUORIDE 0.25 mg/1 mL
INACTIVE INGREDIENTS: SUCROSE; WATER; ASCORBIC ACID; POTASSIUM SORBATE

Tri-Vi-Flor-025mg-Drops

Tri-Vi-Flor

MultiVitamin and Fluoride Supplement - Fruity Flavor

Health Claim

Multivitamin and Fluoride Supplement

Supplement Facts
Serving Size 1 mL • Servings Per Container 50
 |  | % Daily Value
Amount Per 1 mL |  | Infants through 12 months | Children 1 through 3 years of age
vitamin A (as palmitate) | 337.5 mcg | 68% | 113%
vitamin D (as cholecalciferol) | 7.5 mcg | 75% | 50%
folate (from Metafolin®) | 200 mcg DFE | 250% | 153%
fluoride (as sodium fluoride) | 0.25 mg | * | *

*Daily Value not established

Ingredients: Invert Sugar, Water, Ascorbic Acid, Natural Flavoring, Potassium Sorbate

Metafolin® is a registered trademark of Merck KGaA, Darmstadt, Germany

Distributed by: Aytu Therapeutics, LLC
Denver, CO 80237
1-855-298-8246
www.aytubio.com

Dosage and Administration

How to Use the Enclosed

Dropper:

Fill the dropper to the 1 mL line to provide the full daily dosage. Use full dosage, regardless of age or weight, unless your child's doctor recommends a different dosage. Dispense with a single squeeze of the dropper bulb. It is normal for a small amount to remain in the tip.

Dosing Tips:

Drops may be given by dispensing directly into the mouth. Drops may also be mixed with formula, fruit juice, cereal or other foods to increase your child's acceptance.

Shake well before use.

This product comes with a child-resistant cap. Refrigeration not required. After opening, store away from direct sunlight.

Warnings

As with all medicines, keep out of the reach of children.

PRINCIPAL DISPLAY PANEL - Tri-Vi-Flor with 0.25 mg of Fluoride

23594-700-50

Tri-Vi-Flor®

Essential Vitamins for Infants & Toddlers

FRUITY FLAVOR

MULTIVITAMIN AND FLUORIDE SUPPLEMENT

0.25 mg

NOT SUBSTITUTABLE

CONTAINS: METAFOLIN

1 2/3 FL OZ (50 mL)

Aytu BioPharma